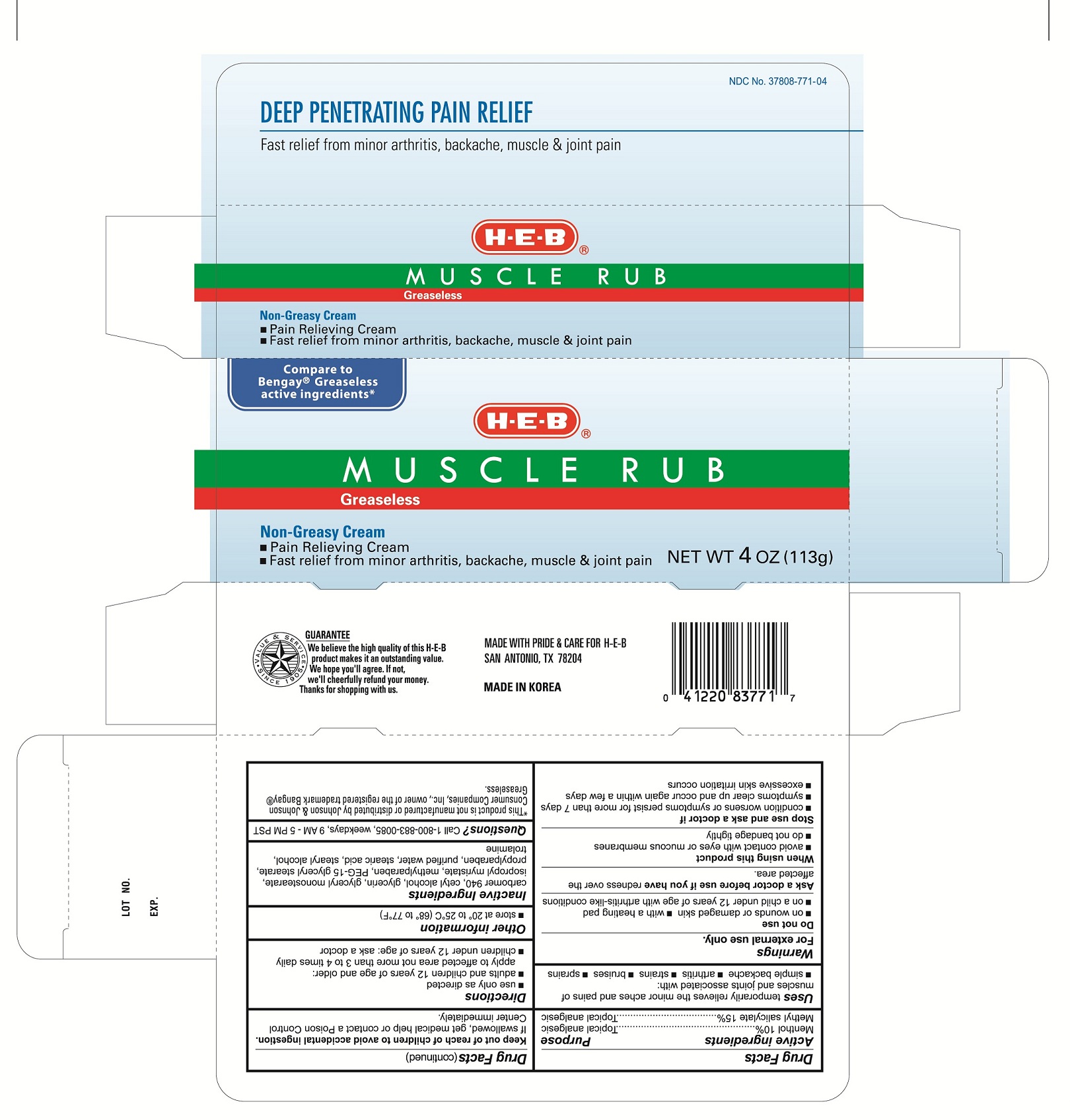 DRUG LABEL: Muscle Rub Greaseless
                        
NDC: 37808-771 | Form: CREAM
Manufacturer: H E B
Category: otc | Type: HUMAN OTC DRUG LABEL
Date: 20110725

ACTIVE INGREDIENTS: Menthol 10 g/100 g; Methyl Salicylate 15 g/100 g
INACTIVE INGREDIENTS: CETYL ALCOHOL; GLYCERYL MONOSTEARATE; ISOPROPYL PALMITATE; METHYLPARABEN; POTASSIUM CETYL PHOSPHATE; STEARIC ACID; STEARYL ALCOHOL; TROLAMINE; WATER

Drug Facts

Active Ingredients

Menthol 10%

Methyl Salicylate15%

Uses

Temporarily relieves the minor aches and pains of muscles and joints associated with:

- simple bachache
- arthritis
- strains
- bruises
- sprains

WARNINGS

For external use only.

Do not use

- on wounds or damaged skin
- with a heating pad
- on a child under 12 years of age with arthritis-like conditions

Ask a doctor before use if you have

redness over the affected area

When using this product

- avoid contact with eyes or mucous membranes
- do not bandage tightly

Stop use and ask a doctor if

- condition worsens or symptoms persist for more than 7 days
- symptoms clear up and occur again within a few days
- excessive skin irritation occurs

Keep out of reach of children to avoid accidental ingestion.

If swallowed, get medical help or contact a Poison Control Center immediately

Directions

- Use only as directed
- adults and children 12 years of age and older:

apply to affected area not more than 3 to 4 times daily

- children under 12 years of age: ask a doctor

Other information

- Store at 20° to 25°C (68°to 77°F)

Inactive Ingredients

carbomer, cetyl alcohol, glyceryl stearate se, isopropyl palmitate, methylparaben, potassium cetyl phophate, propylparabe, stearic acid, stearyl alcohol, trolamine, water

Questions?

call 1-800-883-0085, weekdays, 9AM -5PM PST

PURPOSE

Topical analgesic

Topical analgesic

carton imagae

Enter section text here